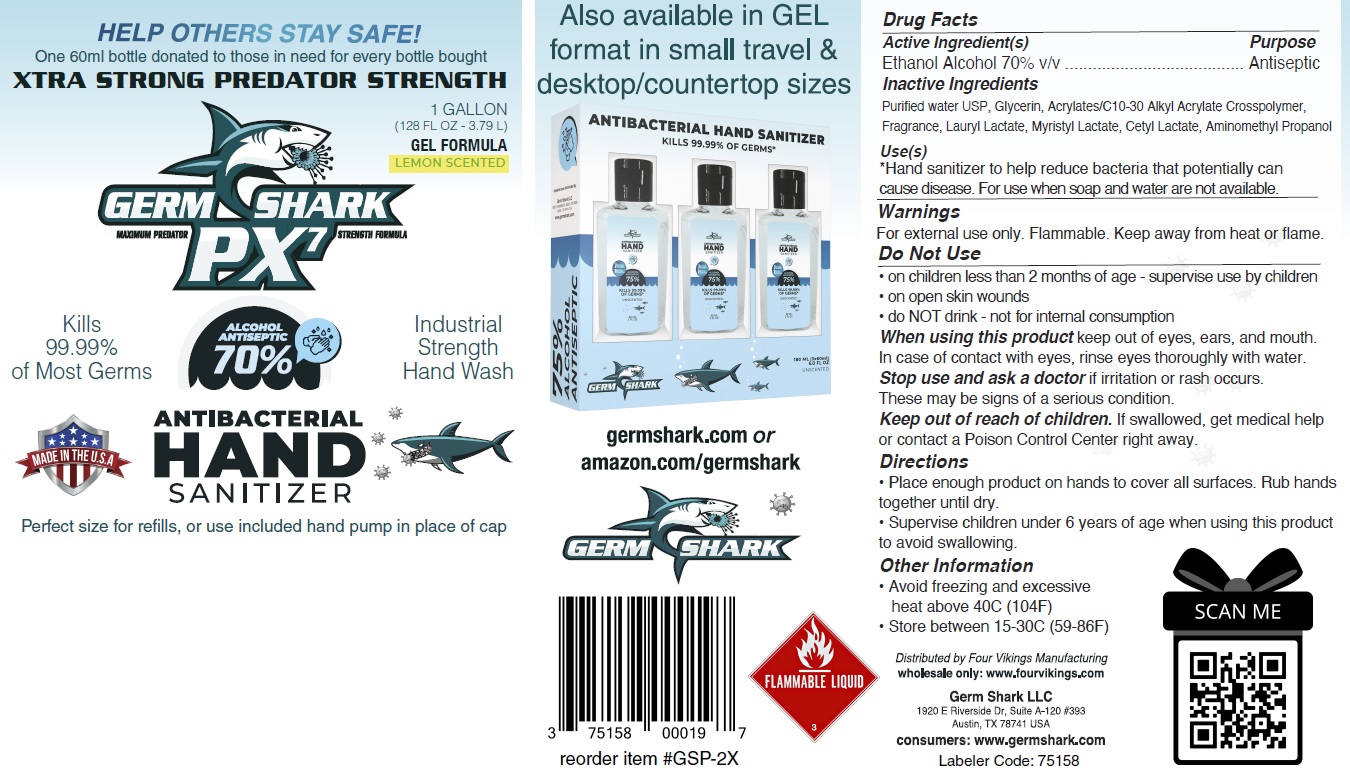 DRUG LABEL: Germ Shark PX7 Antibacterial Hand Sanitizer Lemon Scented
NDC: 75158-005 | Form: GEL
Manufacturer: Germ Shark, LLC
Category: otc | Type: HUMAN OTC DRUG LABEL
Date: 20201013

ACTIVE INGREDIENTS: ALCOHOL 0.7 mL/1 mL
INACTIVE INGREDIENTS: WATER; GLYCERIN; CARBOMER INTERPOLYMER TYPE A (ALLYL SUCROSE CROSSLINKED); LAURYL LACTATE; MYRISTYL LACTATE; CETYL LACTATE; AMINOMETHYLPROPANOL

Germ Shark PX7 Antibacterial Hand Sanitizer Gel Lemon Scented

Active Ingredient(s)

Ethanol Alcohol 70% v/v

Purpose

Antiseptic

Inactive Ingredients

Purified water USP, Glycerin, Acrylates/C10-30 Alkyl Acrylate Crosspolymer, Fragrance, Lauryl Lactate, Myristyl Lactate, Cetyl Lactate, Aminomethyl Propanol

Use(s)

*Hand sanitizer to help reduce bacteria that potentially can cause disease. For use when soap and water are not available.

Warnings

For external use only. Flammable. Keep away from heat or flame.

Do Not Use

• on children less than 2 months of age - supervise use by children
• on open skin wounds
• do NOT drink - not for internal consumption

When using this product

keep out of eyes, ears, and mouth. In case of contact with eyes, rinse eyes thoroughly with water.

Stop use and ask a doctor

if irritation or rash occurs. These may be signs of a serious condition.

Keep out of reach of children.

If swallowed, get medical help or contact a Poison Control Center right away.

Directions

• Place enough product on hands to cover all surfaces. Rub hands together until dry.
• Supervise children under 6 years of age when using this product to avoid swallowing.

Other Information

• Avoid freezing and excessive heat above 40C (104F)
• Store between 15-30C (59-86F)